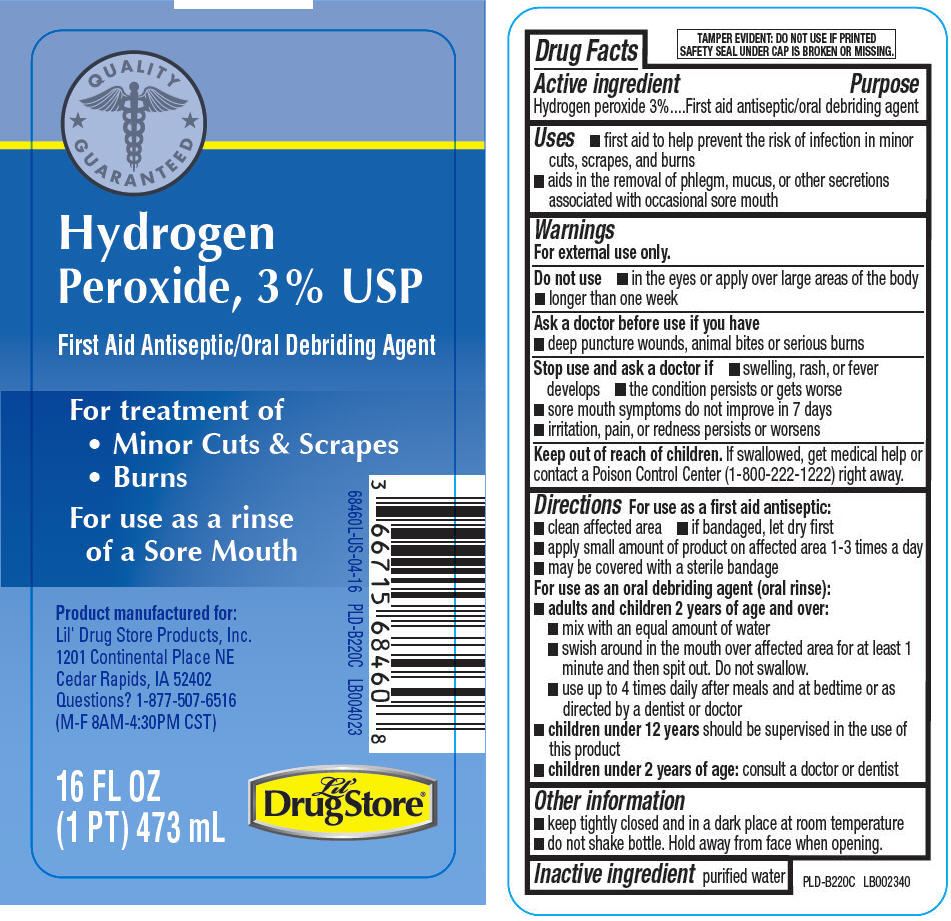 DRUG LABEL: Hydrogen Peroxide
NDC: 66715-6846 | Form: LIQUID
Manufacturer: Lil' Drug Store Products, Inc
Category: otc | Type: HUMAN OTC DRUG LABEL
Date: 20241231

ACTIVE INGREDIENTS: HYDROGEN PEROXIDE 3 mL/100 mL
INACTIVE INGREDIENTS: WATER

Lil' Drug Store® Hydrogen Peroxide, 3%

Drug Facts

Active ingredient

Hydrogen peroxide 3%

Purpose

First aid antiseptic/oral debriding agent

Uses

- first aid to help prevent the risk of infection in minor cuts, scrapes, and burns
- aids in the removal of phlegm, mucus, or other secretions associated with occasional sore mouth

Warnings

For external use only.

Do not use

- in the eyes or apply over large areas of the body
- longer than one week

Ask a doctor before use if you have

- deep puncture wounds, animal bites or serious burns

Stop use and ask a doctor if

- swelling, rash, or fever develops
- the condition persists or gets worse
- sore mouth symptoms do not improve in 7 days
- irritation, pain, or redness persists or worsens

Keep out of reach of children. If swallowed, get medical help or contact a Poison Control Center (1-800-222-1222) right away.

Directions

For use as a first aid antiseptic:

- clean affected area
- if bandaged, let dry first
- apply small amount of product on affected area 1-3 times a day
- may be covered with a sterile bandage

For use as an oral debriding agent (oral rinse):

- adults and children 2 years of age and over:
  - mix with an equal amount of water
  - swish around in the mouth over affected area for at least 1 minute and then spit out. Do not swallow.
  - use up to 4 times daily after meals and at bedtime or as directed by a dentist or doctor
- children under 12 years should be supervised in the use of this product
- children under 2 years of age: consult a doctor or dentist

Other information

- keep tightly closed and in a dark place at room temperature
- do not shake bottle. Hold away from face when opening.

Inactive ingredient

purified water

Questions?

1-877-507-6516
(M-F 8AM-4:30PM CST)

PRINCIPAL DISPLAY PANEL - 473 mL Bottle Label

QUALITY
GUARANTEED

Hydrogen
Peroxide, 3% USP

First Aid Antiseptic/Oral Debriding Agent

For treatment of

- Minor Cuts & Scrapes
- Burns

For use as a rinse
of a Sore Mouth

Product manufactured for:
Lil' Drug Store Products, Inc.
1201 Continental Place NE
Cedar Rapids, IA 52402
Questions? 1-877-507-6516
(M-F 8AM-4:30PM CST)

16 FL OZ
(1 PT) 473 mL

Lil'
DrugStore®

68460L-US-04-16
PLD-B220C
LB004023